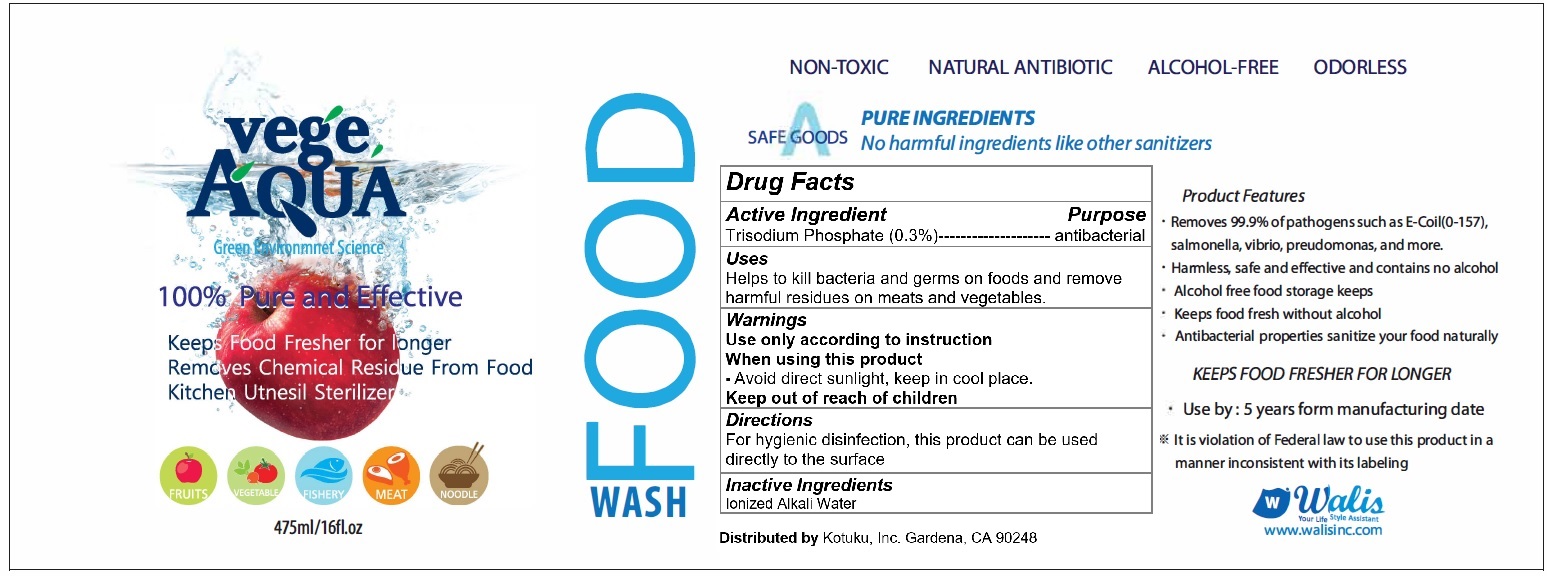 DRUG LABEL: VEGE AQUA
NDC: 70610-104 | Form: LIQUID
Manufacturer: KOTUKU INC.
Category: otc | Type: HUMAN OTC DRUG LABEL
Date: 20180813

ACTIVE INGREDIENTS: SODIUM PHOSPHATE, TRIBASIC, DODECAHYDRATE 1.425 g/475 mL
INACTIVE INGREDIENTS: WATER

VEGE AQUA